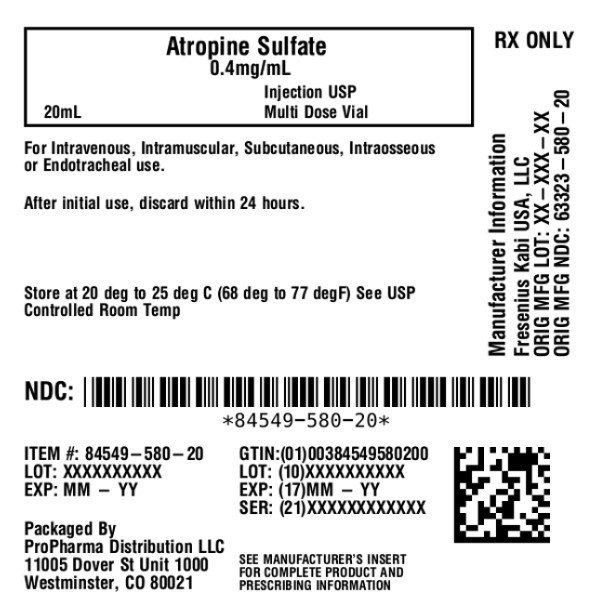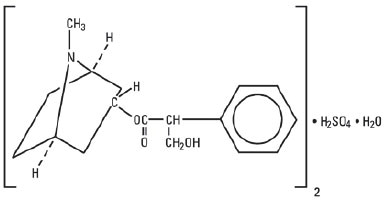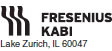 DRUG LABEL: Atropine Sulfate
NDC: 84549-580 | Form: INJECTION, SOLUTION
Manufacturer: ProPharma Distribution
Category: prescription | Type: HUMAN PRESCRIPTION DRUG LABEL
Date: 20251218

ACTIVE INGREDIENTS: ATROPINE SULFATE 0.4 mg/1 mL
INACTIVE INGREDIENTS: SODIUM CHLORIDE; BENZYL ALCOHOL; SULFURIC ACID; WATER

HIGHLIGHTS OF PRESCRIBING INFORMATION

These highlights do not include all the information needed to use ATROPINE SULFATE INJECTION safely and effectively. See full prescribing information for ATROPINE SULFATE INJECTION. ATROPINE SULFATE injection, for intravenous, intramuscular, subcutaneous, intraosseous or endotracheal use.
Initial U.S. Approval: 1960

1 INDICATIONS AND USAGE

Atropine is a muscarinic antagonist indicated for temporary blockade of severe or life threatening muscarinic effects. (1)

2 DOSAGE AND ADMINISTRATION

• Dosage is individualized by use, refer to the full prescribing information for recommended adult and pediatric dosages (2.2, 2.3).
• Patients with Ischemic Heart Disease: Do not exceed 0.04 mg/kg. (2.4, 5.2)

3 DOSAGE FORMS AND STRENGTHS

Injection: 8 mg per 20 mL (0.4 mg per mL) multiple dose glass vial (3)

4 CONTRAINDICATIONS

None. (4)

5 WARNINGS AND PRECAUTIONS

Hypersensitivity (5.1)
Worsening of Ischemic Heart Disease (5.2)
Acute Glaucoma (5.3)
Pyloric obstruction (5.4)
Complete urinary retention (5.5)
Viscid plugs (5.6)

6 ADVERSE REACTIONS

Most adverse reactions are directly related to atropine’s antimuscarinic action. Dryness of the mouth, blurred vision, photophobia and tachycardia commonly occur with chronic administration of therapeutic doses. (6)

To report SUSPECTED ADVERSE REACTIONS, contact Fresenius Kabi USA, LLC at 1-800-551-7176 or FDA at 1-800-FDA-1088 or www.fda.gov/medwatch.

7 DRUG INTERACTIONS

Mexiletine: Decreases rate of mexiletine absorption. (7.1)

FULL PRESCRIBING INFORMATION

1 INDICATIONS AND USAGE

Atropine is indicated for temporary blockade of severe or life threatening muscarinic effects, e.g., as an antisialagogue, an antivagal agent, an antidote for organophosphorus, carbamate, or muscarinic mushroom poisoning, and to treat symptomatic bradycardia.

2 DOSAGE AND ADMINISTRATION

2.1 General Administration

Inspect parenteral drug products for particulate matter and discoloration prior to administration, whenever solution and container permit. Do not administer unless solution is clear and seal is intact. After initial use, discard unused portion within 24 hours.
Intravenous administration is usually preferred, but subcutaneous, intramuscular, endotracheal, and intraosseous administration are possible.

2.2 Adult Dosage

Table 1: Recommended Dosage in Adult Patients

Use | Initial Dose | Continued Treatment
Antisialagogue or other antivagal (preanesthesia and during surgery) | 0.5 to 1 mg IV/IM/SC 30-60 minutes preoperatively | Repeat as needed every 4-6 hours. Maximum Total Dose 3 mg
Organophosphorus, carbamate or muscarinic mushroom poisoning | 1 to 6 mg IV/IM/ET depending on severity of symptoms | Repeat as needed every 3 to 5 minutes Dose may be doubled with each administration until response (reduced bronchospasm, improved oxygenation and drying of pulmonary secretions). Maintenance Dose:Administer 10% to 20% of the loading dose required for response as a continuous infusion per hour and titrate. Maximum Total Dose: No maximum total dose.
Symptomatic bradycardia* | 0.5 mg IV/IM or 1 to 2 mg ET by diluting in no more than 10 mL sterile water for injection or 0.9% sodium chloride | As needed every 3 to 5 minutes Maximum Total Dose 3 mg
IV=intravenous; IM=intramuscular; SC=subcutaneous; ET=endotracheal
*Do not rely on atropine in type II second-degree or third-degree AV block with wide QRS complexes because these bradyarrhythmias are not likely to be responsive to reversal of cholinergic effects by atropine. Atropine has no effect on bradycardia in patients with transplanted hearts.

2.3 Pediatric Dosage

Table 2: Recommended Dosage in Pediatric Patients

Use | Initial Dose | Continued Treatment
Antisialagogue or other antivagal (preanesthesia and during surgery)* | 0.02 mg/kg IV/IM/SC 30-60 minutes preoperatively | Repeat as needed every 4-6 hours.; Maximum Single Dose Less than 12 years old:0.5 mg 12 years and older:1 mg; Maximum Total Dose Less than 12 years old:1 mg 12 years and older:2 mg
Organophosphorus, carbamate, or muscarinic mushroom poisoning | 0.02 to 0.06 mg/kg IV/IM/IO/ET | Repeat as needed every 5 minutes Dose may be doubled with each administration until response (reduced bronchospasm, improved oxygenation and drying of pulmonary secretions). Maintenance Dose:Administer 10% to 20% of the loading dose required for response as a continuous infusion per hour and titrate as needed. Maximum Total Dose: No maximum total dose.
Symptomatic bradycardia due to increased vagal tone or primary AV conduction block (not secondary to hypoxia) * * | 0.02 mg/kg IV/IO or 0.04 to 0.06 mg/kg via endotracheal tube followed by 1 to 5 mL flush of normal saline followed by 5 ventilations | Repeat as needed every 5 minutes Maximum Single Dose Less than12 years old:0.5 mg 12 years and older:1 mg
IV=intravenous; IM=intramuscular; SC=subcutaneous; IO=intraosseous; ET=endotracheal; *Available evidence does not support the routine use of atropine in emergency intubation of critically ill infants and children except in specific emergency intubations when there is higher risk of bradycardia ** Atropine has no effect on bradycardia in patients with transplanted hearts.

2.4 Dosing in Patients with Ischemic Heart Disease

Limit the total dose of atropine sulfate to 0.03 to 0.04 mg/kg [see Warnings and Precautions (5.2)].

3 DOSAGE FORMS AND STRENGTHS

Atropine Sulfate Injection, USP, 8 mg per 20 mL (0.4 mg per mL), is a non-pyrogenic, isotonic, clear solution and is supplied in a multiple dose glass vial.

4 CONTRAINDICATIONS

None.

5 WARNINGS AND PRECAUTIONS

5.1 Hypersensitivity

Atropine may cause anaphylaxis.

5.2 Worsening of Ischemic Heart Disease

In patients with ischemic heart disease, the total dose should be restricted to 2 to 3 mg (maximum 0.03 to 0.04 mg/kg) to avoid atropine-induced tachycardia, increased myocardial oxygen demand and the potential for worsening cardiac ischemia or increasing infarction size.

5.3 Acute Glaucoma

Atropine may precipitate acute glaucoma.

5.4 Pyloric Obstruction

Atropine may convert partial organic pyloric stenosis into complete obstruction.

5.5 Complete Urinary Retention

Atropine may lead to complete urinary retention in patients with prostatic hypertrophy.

5.6 Viscid Plugs

Atropine may cause thickening of bronchial secretions and formation of viscid plugs in patients with chronic lung disease.

5.7 Benzyl Alcohol

The preservative benzyl alcohol has been associated with serious adverse events and death in neonates. The "gasping syndrome"(characterized by central nervous system depression, metabolic acidosis, gasping respirations, and high levels of benzyl alcohol and its metabolites found in the blood and urine) has been associated with benzyl alcohol dosages >99 mg/kg/day in neonates and low-birth weight infants. Additional symptoms may include gradual neurological deterioration, seizures, intracranial hemorrhage, hematologic abnormalities, skin breakdown, hepatic and renal failure, hypotension, bradycardia, and cardiovascular collapse.
Although normal therapeutic doses of this product deliver amounts of benzyl alcohol that are substantially lower than those reported in association with the "gasping syndrome", the minimum amount of benzyl alcohol at which toxicity may occur is not known. Premature and low-birth weight infants may be more likely to develop toxicity. Practitioners administering this and other medications containing benzyl alcohol should consider the combined daily metabolic load of benzyl alcohol from all sources.

6 ADVERSE REACTIONS

The following adverse reactions are described elsewhere in labeling:

- Hypersensitivity (5.1)
- Worsening of Ischemic Heart Disease (5.2)
- Acute Glaucoma (5.3)
- Pyloric Obstruction (5.4)
- Complete Urinary Retention (5.5)
- Viscid Plugs (5.6)

The following adverse reactions have been identified during post-approval use of atropine sulfate. Because these reactions are reported voluntarily from a population of uncertain size, it is not always possible to reliably estimate their frequency or establish a causal relationship to drug exposure.
Most of the side effects of atropine are directly related to its antimuscarinic action. Dryness of the mouth, blurred vision, photophobia and tachycardia commonly occur. Anhidrosis can produce heat intolerance. Constipation and difficulty in micturition may occur. Occasional hypersensitivity reactions have been observed, including serious skin rashes. Paralytic ileus may occur. Exacerbation of reflux has been reported. Larger or toxic doses may produce such central effects as restlessness, tremor, fatigue, locomotor difficulties, delirium, followed by hallucinations, depression, and ultimately, medullary paralysis and death. Large doses can also lead to circulatory collapse. In such cases, blood pressure declines and death due to respiratory failure may ensue following paralysis and coma.

7 DRUG INTERACTIONS

7.1 Mexiletine

Atropine Sulfate Injection decreased the rate of mexiletine absorption without altering the relative oral bioavailability; this delay in mexiletine absorption was reversed by the combination of atropine and intravenous metoclopramide during pretreatment for anesthesia.

8 USE IN SPECIFIC POPULATIONS

8.1 Pregnancy

Risk Summary
Limited available data with Atropine Sulfate Injection use in pregnant women are insufficient to inform a drug associated risk of adverse developmental outcomes (see Data). There are risks to the mother and fetus associated with untreated severe or life-threatening muscarinic events (see Clinical Considerations). Animal reproduction studies have not been conducted with Atropine Sulfate Injection.
The estimated background risk of major birth defects and miscarriage for the indicated population is unknown. All pregnancies have a background risk of birth defect, loss, or other adverse outcomes. In the U.S. general population, the estimated background risk of major birth defects and miscarriage in clinically recognized pregnancies is 2-4% and 15-20%, respectively.
Clinical Considerations
Disease-associated maternal and/or embryo/fetal risk
Severe or life-threatening muscarinic events such as acute organophosphate poisoning and symptomatic bradycardia are medical emergencies in pregnancy which can be fatal if left untreated. Life-sustaining therapy for the pregnant woman should not be withheld due to potential concerns regarding the effects of atropine on the fetus.

Data
Human Data
No adequate and well-controlled studies are available regarding use of atropine in pregnant women. In a cohort study of 401 pregnancies in the first trimester and 797 pregnancies in the second or third trimester, atropine use was not associated with an increased risk of congenital malformation. In a surveillance study, 381 newborns were exposed to atropine during the first trimester; 18 major birth defects were observed when 16 were expected. No specific pattern of major birth defects was identified. In another surveillance study of 50 pregnancies in the first trimester, atropine use was not associated with an increased risk of malformations. Methodological limitations of these observational studies including the inability to control for the dosage and timing of atropine exposure, underlying maternal disease, or concomitant maternal drug use, cannot definitively establish or exclude any drug-associated risk during pregnancy.

8.2 Lactation

Risk Summary
Trace amounts of atropine have been reported in human milk after oral intake. There are no available data on atropine levels in human milk after intravenous injection, the effects on the breastfed infant, or the effects on milk production. The lack of clinical data during lactation precludes a clear determination of the risk of atropine to an infant during lactation.

Clinical Considerations
Minimizing exposure
The elimination half-life of atropine is more than doubled in children less than 2 years of age [see Clinical Pharmacology (12.3)].To minimize potential infant exposure to Atropine Sulfate Injection, a woman may pump and discard her milk for 24 hours after use before resuming to breastfeed her infant.

8.5 Geriatric Use

An evaluation of current literature revealed no clinical experience identifying differences in response between elderly and younger patients. In general, dose selection for an elderly patient should be cautious, usually starting at the low end of the dosing range, reflecting the greater frequency of decreased hepatic, renal, or cardiac function, and of concomitant disease or other drug therapy.

10 OVERDOSAGE

Excessive dosing may cause palpitation, dilated pupils, difficulty in swallowing, hot dry skin, thirst, dizziness, restlessness, tremor, fatigue and ataxia. Toxic doses lead to restlessness and excitement, hallucinations, delirium and coma. Depression and circulatory collapse occur only with severe intoxication. In such cases, blood pressure declines and death due to respiratory failure may ensue following paralysis and coma.
The fatal adult dose of atropine is not known. In pediatric populations, 10 mg or less may be fatal.
In the event of toxic overdosage, a short acting barbiturate or diazepam may be given as needed to control marked excitement and convulsions. Large doses for sedation should be avoided because central depressant action may coincide with the depression occurring late in atropine poisoning. Central stimulants are not recommended.
Physostigmine, given as an atropine antidote by slow intravenous injection of 1 to 4 mg (0.5 to 1 mg in pediatric populations), rapidly abolishes delirium and coma caused by large doses of atropine. Since physostigmine is rapidly destroyed, the patient may again lapse into coma after one to two hours, and repeated doses may be required.
Artificial respiration with oxygen may be necessary. Ice bags and alcohol sponges help to reduce fever, especially in pediatric populations.
Atropine is not removed by dialysis.

11 DESCRIPTION

Atropine Sulfate Injection, USP is a sterile, nonpyrogenic, isotonic, clear solution of atropine sulfate in water for injection with sodium chloride sufficient to render the solution isotonic. It is administered parenterally by subcutaneous, intramuscular or intravenous injection.

Each mL contains atropine sulfate, 0.4 mg; benzyl alcohol, 9 mg; sodium chloride 9 mg. May contain sulfuric acid for pH adjustment. pH 3.5 (3.0 to 3.8).

Sodium chloride added to render the solution isotonic for injection of the active ingredient is present in amounts insufficient to affect serum electrolyte balance of sodium (Na^+) and chloride (Cl^-) ions.

Atropine Sulfate, USP is chemically designated lα H, 5α H-Tropan-3-α-ol (±)-tropate (ester), sulfate (2:1) (salt) monohydrate, (C17H23NO3)2· H2SO4· H2O, colorless crystals or white crystalline powder very soluble in water. It has the following structural formula:

Atropine, a naturally occurring belladonna alkaloid, is a racemic mixture of equal parts of d- and 1-hyocyamine, whose activity is due almost entirely to the levo isomer of the drug.

Sodium Chloride, USP is chemically designated NaCl, a white crystalline powder freely soluble in water.

12 CLINICAL PHARMACOLOGY

12.1 Mechanism of Action

Atropine is an antimuscarinic agent since it antagonizes the muscarine-like actions of acetylcholine and other choline esters.

Atropine inhibits the muscarinic actions of acetylcholine on structures innervated by postganglionic cholinergic nerves, and on smooth muscles which respond to endogenous acetylcholine but are not so innervated. As with other antimuscarinic agents, the major action of atropine is a competitive or surmountable antagonism which can be overcome by increasing the concentration of acetylcholine at receptor sites of the effector organ (e.g., by using anticholinesterase agents which inhibit the enzymatic destruction of acetylcholine). The receptors antagonized by atropine are the peripheral structures that are stimulated or inhibited by muscarine (i.e., exocrine glands and smooth and cardiac muscle). Responses to postganglionic cholinergic nerve stimulation also may be inhibited by atropine but this occurs less readily than with responses to injected (exogenous) choline esters.

12.2 Pharmacodynamics

Atropine-induced parasympathetic

inhibition may be preceded by a transient phase of stimulation, especially on the heart where small doses first slow the rate before characteristic tachycardia develops due to paralysis of vagal control. Atropine exerts a more potent and prolonged effect on heart, intestine and bronchial muscle than scopolamine, but its action on the iris, ciliary body and certain secretory glands is weaker than that of scopolamine. Unlike the latter, atropine in clinical doses does not depress the central nervous system but may stimulate the medulla and higher cerebral centers. Although mild vagal excitation occurs, the increased respiratory rate and (sometimes) increased depth of respiration produced by atropine are more probably the result of bronchiolar dilatation. Accordingly, atropine is an unreliable respiratory stimulant and large or repeated doses may depress respiration.
Adequate doses of atropine abolish various types of reflex vagal cardiac slowing or asystole. The drug also prevents or abolishes bradycardia or asystole produced by injection of choline esters, anticholinesterase agents or other parasympathomimetic drugs, and cardiac arrest produced by stimulation of the vagus. Atropine also may lessen the degree of partial heart block when vagal activity is an etiologic factor. In some patients with complete heart block, the idioventricular rate may be accelerated by atropine; in others, the rate is stabilized. Occasionally a large dose may cause atrioventricular (A-V) block and nodal rhythm.
Atropine in clinical doses counteracts the peripheral dilatation and abrupt decrease in blood pressure produced by choline esters. However, when given by itself, atropine does not exert a striking or uniform effect on blood vessels or blood pressure. Systemic doses slightly raise systolic and lower diastolic pressures and can produce significant postural hypotension. Such doses also slightly increase cardiac output and decrease central venous pressure. Occasionally, therapeutic doses dilate cutaneous blood vessels, particularly in the "blush" area (atropine flush), and may cause atropine "fever" due to suppression of sweat gland activity in infants and small children.
The effects of intravenous atropine on heart rate (maximum heart rate) and saliva flow (minimum flow) after I.V. administration (rapid, constant infusion over 3 min.) are delayed by 7 to 8 minutes after drug administration and both effects are non-linearly related to the amount of drug in the peripheral compartment. Changes in plasma atropine levels following intramuscular administration (0.5 to 4 mg doses) and heart rate are closely overlapped but the time course of the changes in atropine levels and behavioral impairment indicates that pharmacokinetics is not the primary rate-limiting mechanism for the central nervous system effect of atropine.

12.3 Pharmacokinetics

Absorption
After intramuscular administration, atropine is absorbed with peak concentration occurring at 30 min following injection.

Effects of exercise:
Exercise following intramuscular administration of atropine significantly increases the absorption of atropine due to increased perfusion in the muscle, with an increase in AUC by approximately 20% and Cmax by approximately 80%.

Distribution
Atropine is distributed throughout the body. Atropine’s plasma protein binding is about 44% and saturable in the 2 to 20 mcg/mL concentration range.

Elimination
The pharmacokinetics of atropine is nonlinear after intravenous administration of 0.5 to 4 mg. Atropine disappears from the blood following injection with a plasma half-life of about 2-4 hours. Much of the drug is destroyed by enzymatic hydrolysis, particularly in the liver, with 13 to 50% is excreted unchanged in the urine.

Metabolism
The major metabolites of atropine are noratropine, atropin-n-oxide, tropine, and tropic acid. The metabolism of atropine is inhibited by organophosphate pesticides.

Specific Populations

Pregnant Women
Atropine readily crosses the placental barrier and enters the fetal circulation, but is not found in amniotic fluid.
Nursing Mother
Traces are found in various secretions, including milk.

Pediatric and Geriatric Patients
The elimination half-life of atropine is more than doubled in children under two years, and the elderly (> 65 years old) compared to other age groups.

13 NONCLINICAL TOXICOLOGY

13.1 Carcinogenesis, Mutagenesis, Impairment of Fertility

Studies have not been performed to evaluate the carcinogenic or mutagenic potential of atropine or its potential to affect fertility adversely.

16 HOW SUPPLIED/STORAGE AND HANDLING

Atropine Sulfate Injection, USP is a non-pyrogenic, isotonic, clear solution and is supplied as follows:

Single Vial
NDC# 84549-580-20
Description
8 mg per 20 mL
(0.4 mg per mL)
Multiple-dose vial

Store at 20° to 25°C (68° to 77°F) [see USP Controlled Room Temperature]. After initial use, store between 20° to 25°C (68° to 77°F) and discard within 24 hours.

www.fresenius-kabi.com/us
451539
Issued: March 2018